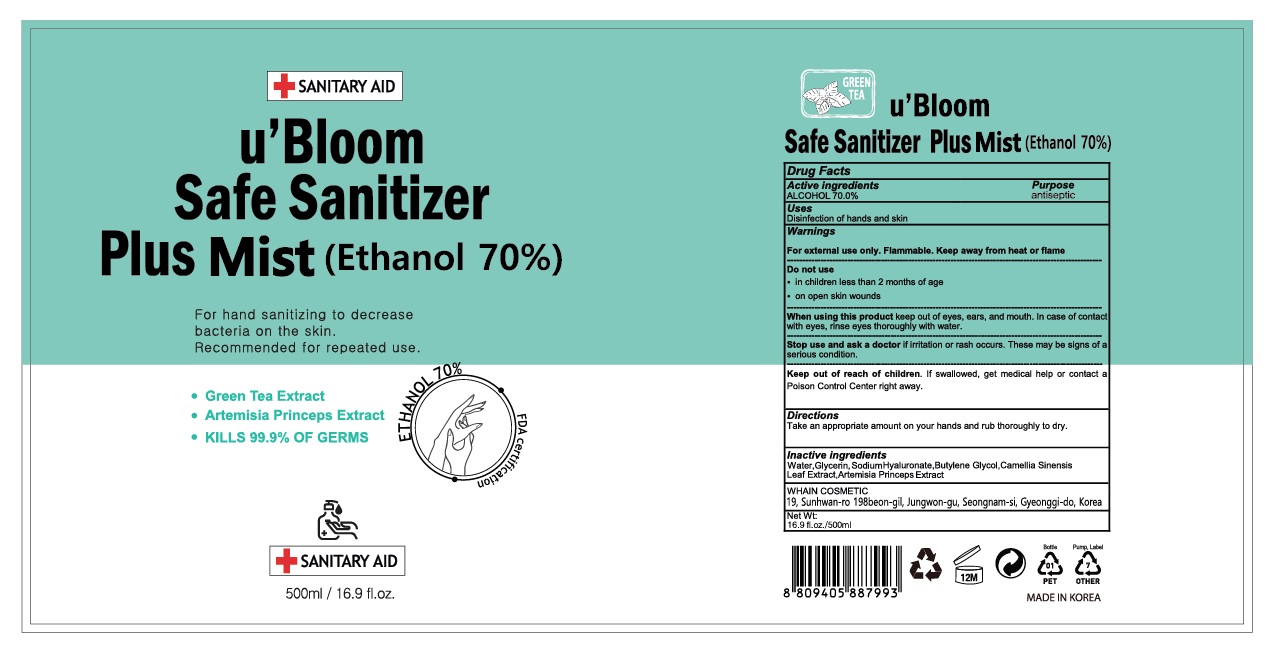 DRUG LABEL: uBloom Safe Sanitizer Plus Mist
NDC: 73823-507 | Form: SPRAY
Manufacturer: WHAIN COSMETIC
Category: otc | Type: HUMAN OTC DRUG LABEL
Date: 20200517

ACTIVE INGREDIENTS: ALCOHOL 350 mL/500 mL
INACTIVE INGREDIENTS: GLYCERIN; HYALURONATE SODIUM; BUTYLENE GLYCOL; WATER; ARTEMISIA PRINCEPS LEAF; GREEN TEA LEAF

[WHAIN COSMETIC] u'Bloom Safe Sanitizer Plus Mist 500 ml : 73823-507